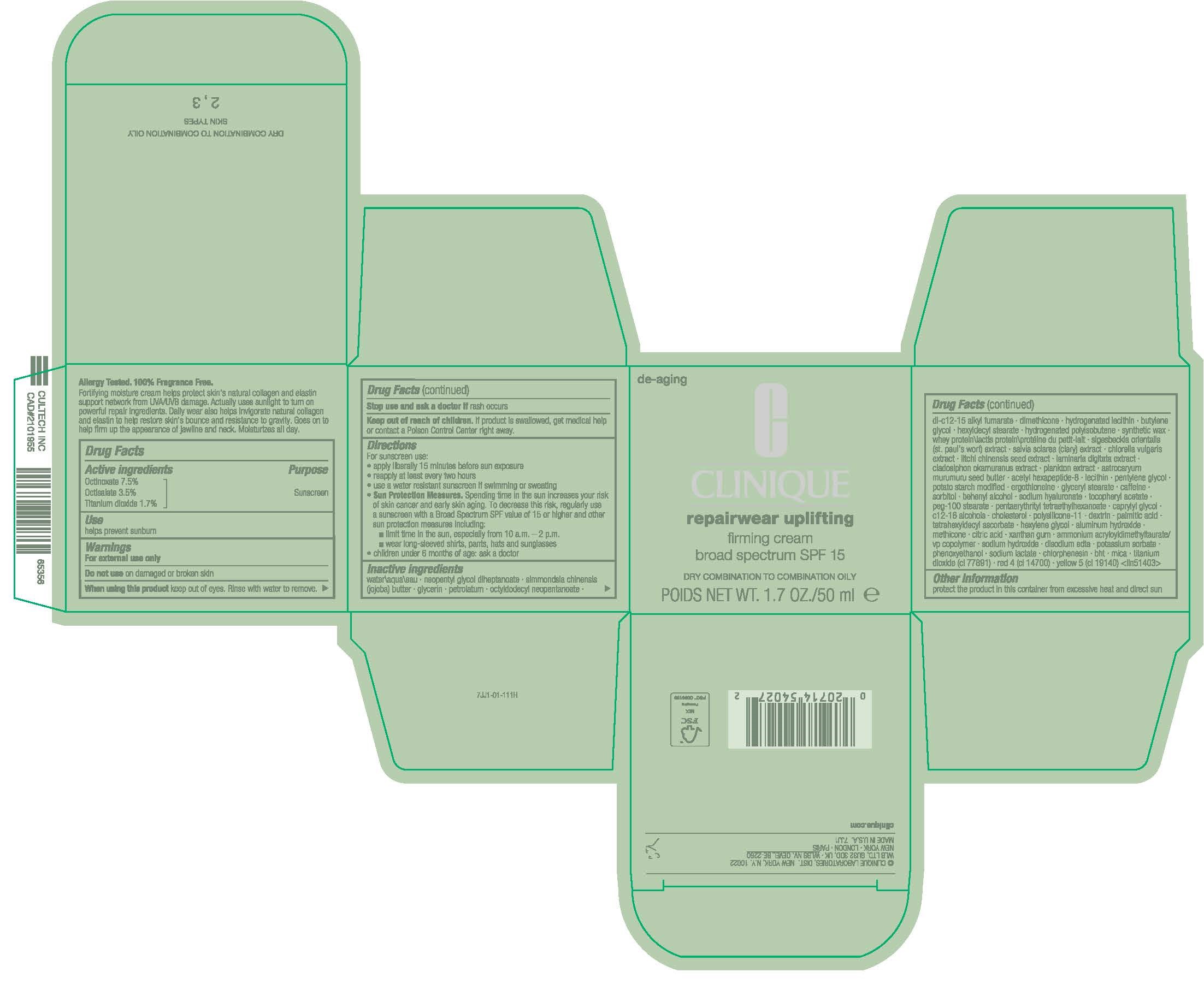 DRUG LABEL: REPAIRWEAR UPLIFTING FIRMING
NDC: 49527-022 | Form: CREAM
Manufacturer: CLINIQUE LABORATORIES LLC
Category: otc | Type: HUMAN OTC DRUG LABEL
Date: 20250220

ACTIVE INGREDIENTS: OCTINOXATE 75 mg/1 mL; OCTISALATE 35 mg/1 mL; TITANIUM DIOXIDE 17 mg/1 mL
INACTIVE INGREDIENTS: SODIUM LACTATE; HYDROGENATED SOYBEAN LECITHIN; WHEY; METHICONE (20 CST); DIMETHICONE/VINYL DIMETHICONE CROSSPOLYMER (SOFT PARTICLE); EDETATE DISODIUM ANHYDROUS; WATER; NEOPENTYL GLYCOL DIHEPTANOATE; JOJOBA BUTTER; GLYCERIN; PETROLATUM; OCTYLDODECYL NEOPENTANOATE; DI-C12-15 ALKYL FUMARATE; DIMETHICONE; BUTYLENE GLYCOL; HEXYLDECYL STEARATE; CLARY SAGE; CHLORELLA VULGARIS; LITCHI CHINENSIS SEED; LAMINARIA DIGITATA; CLADOSIPHON OKAMURANUS; ASTROCARYUM MURUMURU SEED BUTTER; ACETYL HEXAPEPTIDE-8; PENTYLENE GLYCOL; ERGOTHIONEINE; GLYCERYL MONOSTEARATE; CAFFEINE; SORBITOL; DOCOSANOL; HYALURONATE SODIUM; .ALPHA.-TOCOPHEROL ACETATE; PEG-100 STEARATE; PENTAERYTHRITYL TETRAETHYLHEXANOATE; CAPRYLYL GLYCOL; C12-16 ALCOHOLS; CHOLESTEROL; ICODEXTRIN; PALMITIC ACID; TETRAHEXYLDECYL ASCORBATE; HEXYLENE GLYCOL; CITRIC ACID MONOHYDRATE; XANTHAN GUM; AMMONIUM ACRYLOYLDIMETHYLTAURATE/VP COPOLYMER; SODIUM HYDROXIDE; POTASSIUM SORBATE; PHENOXYETHANOL; FD&C RED NO. 4; FD&C YELLOW NO. 5; MICA; HYDROGENATED POLYBUTENE (1300 MW); STARCH, POTATO; SIGESBECKIA ORIENTALIS FLOWERING TOP; LECITHIN, SOYBEAN; SYNTHETIC WAX (1200 MW); BHT; ALUMINUM HYDROXIDE; CHLORPHENESIN

REPAIRWEAR UPLIFTING FIRMING
BROAD SPECTUM SPF 15 - NORMAL COMBO TO COMBINATION OILY

Drug Facts

Active ingredients

Octinoxate 7.5%
Octisalate 3.5%
Titanium dioxide 1.7%

Purpose

Sunscreen

Use

helps prevent sunburn

Warnings

For external use only

Do not use on damaged or broken skin

When using this product keep out of eyes. Rinse with water to remove.

Stop use and ask a doctor if rash occurs

Keep out of reach of children. If product is swallowed, get medical help or contact a Poison Control Center right away.

Directions

For sunscreen use:

- apply liberally 15 minutes before sun exposure
- reapply at least every two hours
- use a water resistant sunscreen if swimming or sweating
- Sun Protection Measures. Spending time in the sun increases your risk of skin cancer and early skin aging. To decrease this risk, regularly use a sunscreen with a Broad Spectrum SPF value of 15 or higher and other sun protection measures including:
  - limit time in the sun, especially from 10 a.m. – 2 p.m.
  - wear long-sleeved shirts, pants, hats and sunglasses
- children under 6 months of age: ask a doctor

Inactive ingredients

water\aqua\eau,neopentyl glycol diheptanoate,simmondsia chinensis (jojoba) butter,glycerin,petrolatum,octyldodecyl neopentanoate,di-c12-15 alkyl fumarate,dimethicone,hydrogenated lecithin,butylene glycol,hexyldecyl stearate,hydrogenated polyisobutene,synthetic wax,whey protein\lactis protein\protéine du petit-lait,sigesbeckia orientalis (st. paul's wort) extract,salvia sclarea (clary) extract,chlorella vulgaris extract,litchi chinensis seed extract,laminaria digitata extract,cladosiphon okamuranus extract,plankton extract,astrocaryum murumuru seed butter,acetyl hexapeptide-8,lecithin,pentylene glycol,potato starch modified,ergothioneine,glyceryl stearate,caffeine,sorbitol,behenyl alcohol,sodium hyaluronate,tocopheryl acetate,peg-100 stearate,pentaerythrityl tetraethylhexanoate,caprylyl glycol,c12-16 alcohols,cholesterol,polysilicone-11,dextrin,palmitic acid,tetrahexyldecyl ascorbate,hexylene glycol,aluminum hydroxide,methicone,citric acid,xanthan gum,ammonium acryloyldimethyltaurate/vp copolymer,sodium hydroxide,disodium edta,potassium sorbate,phenoxyethanol,sodium lactate,chlorphenesin,bht,mica,titanium dioxide (ci 77891),red 4 (ci 14700),yellow 5 (ci 19140) <iln51403>

Other information

protect the product in this container from excessive heat and direct sun

DIST. N.Y., N.Y. 10022

PRINCIPAL DISPLAY PANEL - 50 mL Jar Carton

C
CLINIQUE

repairwear uplifting

firming cream
broad spectrum SPF 15

DRY COMBINATION TO COMBINATION OILY

POIDS NET WT. 1.7. OZ./50 ml e